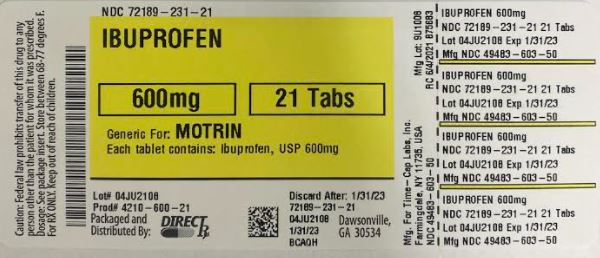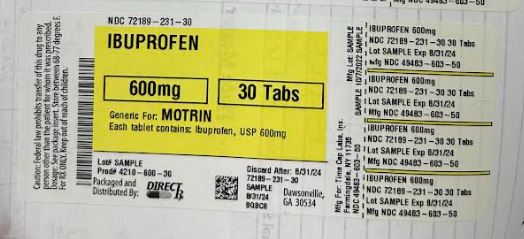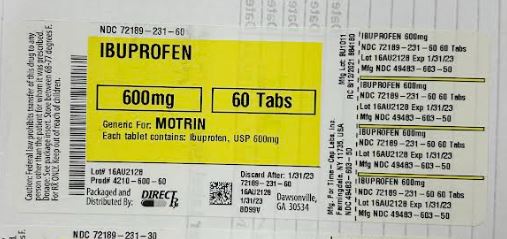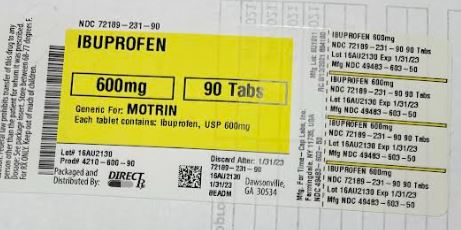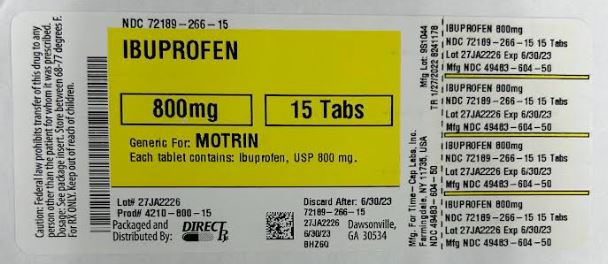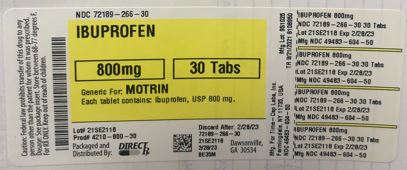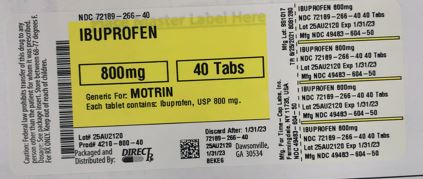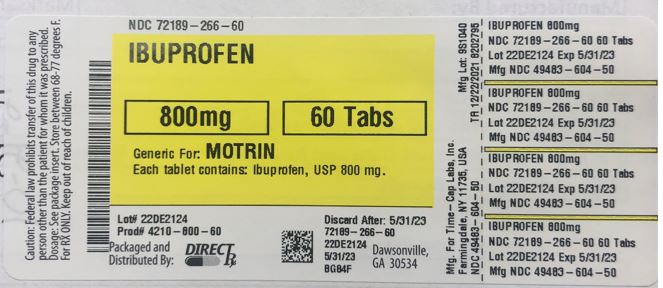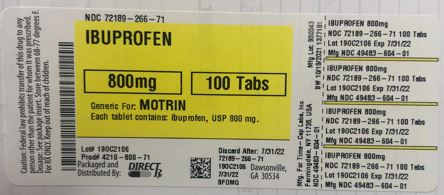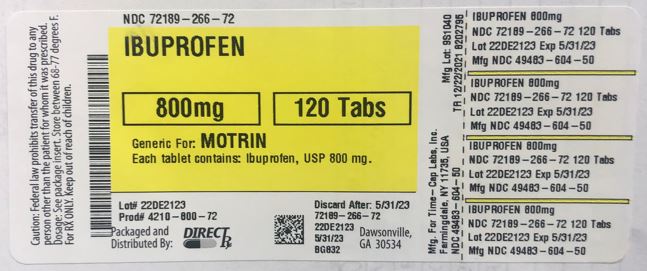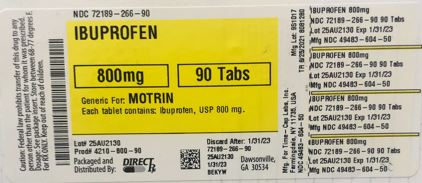 DRUG LABEL: IBUPROFEN
NDC: 72189-266 | Form: TABLET, FILM COATED
Manufacturer: DIRECT RX
Category: prescription | Type: HUMAN PRESCRIPTION DRUG LABEL
Date: 20250120

ACTIVE INGREDIENTS: IBUPROFEN 800 mg/1 1
INACTIVE INGREDIENTS: CROSCARMELLOSE SODIUM; POLYVINYL ALCOHOL, UNSPECIFIED; TITANIUM DIOXIDE; SILICON DIOXIDE; TALC; STARCH, CORN; POLYETHYLENE GLYCOL, UNSPECIFIED; MAGNESIUM STEARATE; CELLULOSE, MICROCRYSTALLINE

IBUPROFEN

MEDICATION GUIDE

[MEDGUIDE IBUPROFEN TABLETS]

HOW SUPPLIED

400mg (white to of white, round, biconvex, film coated tablets debossed with '121' on one side and plain on the other side) Bottles of 100 & 500

HOW SUPPLIED

600mg (white to off white, capsule shaped, biconvex, film coated tablets debossed with '122' on one side and plain on the other side) Bottles of 30, 50, 100 & 500

HOW SUPPLIED

800 mg (white to off-white, capsule shaped, biconvex, film-coated tablets debossed with ‘123’ on one side and plain on other side)